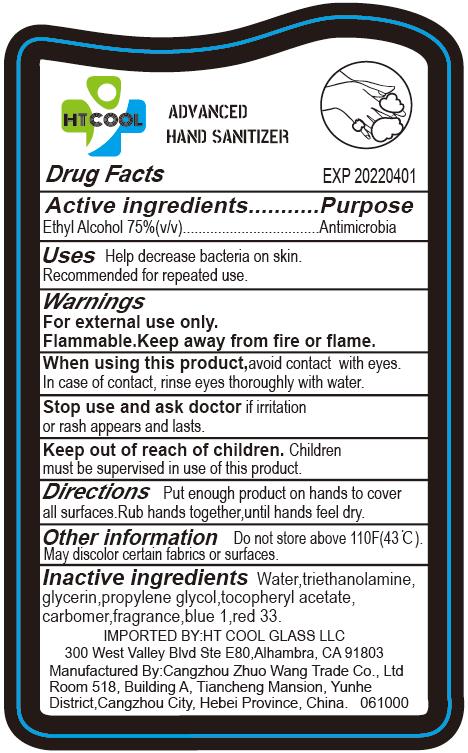 DRUG LABEL: HAND SANITIZER
NDC: 77583-101 | Form: GEL
Manufacturer: HT COOL GLASS LLC
Category: otc | Type: HUMAN OTC DRUG LABEL
Date: 20200531

ACTIVE INGREDIENTS: ALCOHOL 75 mL/100 mL
INACTIVE INGREDIENTS: GLYCERIN; CARBOMER HOMOPOLYMER, UNSPECIFIED TYPE; WATER; HYALURONATE SODIUM; TROLAMINE

HT COOL, Sanitizer, Ethyl alcohol 75%, Liquid

Active Ingredient(s)

Ethyl Alcohol 75% v/v. Purpose: Antimicrobial

Purpose

Antimicrobial

Use

Hand sanitizer to help decrease bacteria on skin.

Recommended for repeated use.

Warnings

For external use only.

Flammable. Keep away from hire or flame.

Do not use

- on children less than 2 months of age
- on open skin wounds

Stop use and ask doctor if irritation or rash appears and lasts.

Keep out of reach of children. Children must be superised in use of this product.

Directions

Put enough product on hands to cover all surfaces. Rub hands together, until hands feel dry.

Other information

Do not store above 110℉(43℃).

May discolor certain fabrics or surfaces.

Inactive ingredients

Glycerol, Sodium hyaluronate, Trolamine, Carbomer, Water.